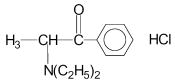 DRUG LABEL: Unknown
Manufacturer: Qualitest Products, Inc.
Category: prescription | Type: HUMAN PRESCRIPTION DRUG LABELING
Date: 20060726
DEA Schedule: CIV

Tepanil Ten-Tab, 75 mg, Controlled Release Tablets (Diethylpropion hydrochloride)

CIV

DESCRIPTION

Diethylpropion hydrochloride, a sympathomimetic agent. Chemically, diethylpropion hydrochloride is 1-phenyl-2-diethylamino-1-propanone hydrochloride.

Structural formula: C13H18NO HCl

Molecular weight: 241.76

Each tablet contains diethylpropion hydrochloride 75 mg in a controlled-release formulation. Diethylpropion hydrochloride tablets also contain: carbomer, mannitol, povidone, tartaric acid and zinc stearate.

Diethylpropion hydrochloride is dispersed in a hydrophilic matrix. On exposure to water the diethylpropion hydrochloride is released at a relatively uniform rate as a result of slow hydration of the matrix. The result is controlled release of the anorexic agent.

CLINICAL PHARMACOLOGY

Diethylpropion hydrochloride is a sympathomimetic amine with some pharmacologic activity similar to that of the prototype drugs of this class used in obesity, the amphetamines. Actions include some central nervous system stimulation and elevation of blood pressure. Tolerance has been demonstrated with all drugs of this class in which these phenomena have been looked for.

Drugs of this class used in obesity are commonly known as “anorectics” or “anorexigenics”. It has not been established, however, that the action of such drugs in treating obesity is primarily one of appetite suppression. Other central nervous system actions or metabolic effects may be involved, for example.

Adult obese subjects instructed in dietary management and treated with “anorectic” drugs lose more weight on the average than those treated with placebo and diet, as determined in relatively short-term clinical trials.

The magnitude of increased weight loss of drug-treated patients over placebo-treated patients averages some fraction of a pound a week. However, individual weight loss may vary substantially from patient to patient. The rate of weight loss is greatest in the first weeks of therapy for both drug and placebo subjects and tends to decrease in succeeding weeks. The possible origins of the increased weight loss due to the various drug effects are not established. The amount of weight loss associated with the use of an “anorectic” drug varies from trial to trial, and the increased weight loss appears to be related in part to variables other than the drug prescribed, such as the physician/investigator relationship, the population treated, and the diet prescribed. Studies do not permit conclusions as to the relative importance of the drug and non-drug factors on weight loss.

The natural history of obesity is measured in years, whereas most studies cited are restricted to a few weeks duration. Thus, the total impact of drug-induced weight loss over that of diet alone is unknown.

Diethylpropion is rapidly absorbed from the GI tract after oral administration and is extensively metabolized through a complex pathway of biotransformation involving N-dealkylation and reduction. Many of these metabolites are biologically active and may participate in the therapeutic action of these drugs. Due to the varying lipid solubilities of these metabolites, their circulating levels are affected by urinary pH. Diethylpropion and/or its active metabolites are believed to cross the blood-brain barrier and the placenta (see Labor and Delivery).

Diethylpropion and its metabolites are excreted mainly by the kidney. It has been reported that between 75-106% of the dose is recovered in the urine within 48 hours after dosing. Using a phosphorescence assay that is specific for basic compounds containing a benzoyl group, the plasma half-life of the aminoketone metabolites is estimated to be between 4 to 6 hours.

The controlled-release characteristics of Diethlpropion have been demonstrated by studies in humans in which plasma levels of diethylpropion-related material were measured by phosphorescence analysis. Plasma levels obtained with the 75 mg Diethylpropion formulation administered once daily indicated a more gradual release than the standard formulation, however, it has not been shown superior in effectiveness to the same dosage of the standard, non-controlled-release formulation.

INDICATIONS AND USAGE

Diethylpropion hydrochloride tablets are indicated in the management of exogenous obesity as a short-term adjunct (a few weeks) in a regiment of weight reduction based on caloric restriction. The usefulness of agents of this class should be measured against possible risk factors inherent in their use such as those described (see CLINICAL PHARMACOLOGY).

CONTRAINDICATIONS

Diethylpropion hydrochloride should not be used in patients with advanced arteriosclerosis, hyperthyroidism, known hypersensitivity or idiosyncrasy to the sympathomimetic amines, glaucoma, severe hypertension, a history of drug abuse, or those in an agitated state (see PRECAUTIONS).

Diethylpropion hydrochloride should not be given during, or within fourteen days following, the administration of monoamine oxidase inhibitors; hypertensive crises may result.

WARNINGS

If tolerance develops, the recommended dose should not be exceeded in an attempt to increase the effect: rather, the drug should be discontinued.

PRECAUTIONS

General Precautions:

Caution is to be exercised in prescribing Diethylpropion hydrochloride for patients with hypertension or with symptomatic cardiovascular disease, including arrhythmias. They should not be administered to patients with severe hypertension. Reports suggest that Diethylpropion hydrochloride may increase convulsions in some epileptics. Therefore, epileptics receiving them should be carefully monitored. Titration of dose or discontinuance of drug may be necessary. The least amount feasible should be prescribed or dispensed at one time to minimize the possibility of an overdose.

Information for Patients:

Diethylpropion hydrochloride may impair the ability of the patient to engage in potentially hazardous activities such as operating machinery or driving a motor vehicle; ambulatory patients should therefore by cautioned accordingly. When central nervous system-active agents are used, consideration must always be given to the possibility of adverse interactions with alcohol.

Drug Interactions:

Antidiabetic drug requirements, i.e., insulin, may be altered in association with the use of Diethylpropion hydrochloride and the concomitant dietary regimen. Concurrent use with general anesthetics may result in arrhythmias. The presser effects of diethylpropion and those of other drugs may be additive when the drugs are used concomitantly; conversely, diethylpropion may interfere with antihypertensive drugs, i.e., guanethidine, a-methyldopa. Concurrent use of phenothiazines may antagonize the anorectic effect of diethylpropion.

Carcinogenesis, Mutagenesis and Impairment of Fertility

Diethylpropion hydrochloride has not been evaluated for carcinogenicity, mutagenicity, or impairment of fertility.

Pregnancy: Teratogenic Effects: - Pregnancy Category B:

Reproduction studies have been performed in rats at doses up to nine times the human dose and have revealed no evidence of impaired fertility or harm to the fetus due to diethylpropion hydrochloride. However, no adequate and well-controlled studies have been conducted in pregnant women. Because animal reproduction studies are not always predictive of human response, this drug should be used during pregnancy only if clearly needed.

Pregnancy: Nonteratogenic Effects:

Abuse during pregnancy may result in withdrawal symptoms in the neonate.

Labor and Delivery:

Diethylpropion hydrochloride has no recognized use during labor and delivery, and its effect during these processes are unknown. Diethylpropion and /or its active metabolites are believed to cross the placenta.

Nursing Mothers:

It is not known whether diethylpropion is excreted in human milk. Because many drugs are excreted in human milk, caution should be used when Diethylpropion hydrochloride is administered to a nursing woman.

Pediatric Use:

Safety and effectiveness in pediatric patients below the age of 16 have not been established.

ADVERSE REACTIONS

The following adverse effects, listed by organ system, have been associated with the use of Diethylpropion hydrochloride.

Cardiovascular:

Precordial pain, arrhythmia, ECG changes (one published report described T-wave changes in the ECG of a healthy young male after ingestion of diethylpropion hydrochloride), tachycardia, elevation of blood pressure, palpitation.

Central Nervous System:

In a few epileptics an increase in convulsive episodes has been reported: dyskinesia, blurred vision, overstimulation, nervousness, restlessness, dizziness, jitteriness, insomnia, anxiety, euphoria, depression, dysphoria, tremor, mydriasis, drowsiness, malaise, headache, and rarely, psychotic episodes at recommended doses.

Gastrointestinal:

Vomiting, diarrhea, abdominal discomfort, dryness of the mouth, unpleasant taste, nausea, constipation.

Allergic:

Urticaria, rash, ecchymosis, erythema.

Endocrine:

Impotence, changes in libido, gynecomastia, menstrual upset.

Hematopoietic System:

Bone marrow depression, agranulocytosis, leukopenia.

Other:

Dysuria, dyspnea, hair loss, muscle pain, increased sweating, polyuria.

DRUG ABUSE AND DEPENDENCE:

Controlled Substance:

Diethylpropion is a schedule IV controlled substance.

Abuse:

Diethylpropion has some chemical and pharmacologic similarities to the amphetamines and other related stimulant drugs that have been extensively abused. The possibility of abuse should be kept in mind when evaluating the desirability of including a drug as part of a weight reduction program. Abuse of amphetamines and related drugs may be associated with varying degrees of psychologic dependence and social dysfunction which, in the case of certain drugs, may be severe. There are reports of patients who have increased the dosage to many times that recommended.

Dependence:

There have been reports of subjects becoming psychologically dependent on diethylpropion. Abrupt cessation following prolonged high dosage administration results in extreme fatigue and mental depression; changes are also noted on the sleep EEG. Manifestations of chronic intoxication with anorectic drugs include severe dermatoses, marked insomnia, irritability, hyperactivity, and personality changes. The most severe manifestation of chronic intoxication is psychosis, often clinically indistinguishable from schizophrenia.

OVERDOSAGE

The reported oral LD50, for diethylpropion hydrochloride in mice is 620 mg/kg. In rats 250 mg/kg and in dogs 225 mg/kg.

Symptoms:

Manifestations of acute overdosage include restlessness, tremor, hyperreflexia, rapid respiration, confusion, assaultiveness, hallucinations, panic states.

Fatigue and depression usually follow the central stimulation.

Cardiovascular effects include arrhythmias, hypertension or hypotension, and circulatory collapse. Gastrointestinal symptoms include nausea, vomiting, diarrhea, and abdominal cramps. Overdose of pharmacologically similar compounds has resulted in fatal poisoning, usually terminating in convulsions and coma.

Treatment:

Management of acute Diethylpropion hydrochloride intoxication is largely symptomatic and includes lavage and sedation with a barbiturate. Experience with hemodialysis or peritoneal dialysis is inadequate to permit recommendation in this regard: Intravenous phentolamine (Regitine®) has been suggested on pharmacologic grounds for possible acute, severe hypertension. If this complicates diethylpropion hydrochloride overdosage.

DOSAGE AND ADMINISTRATION

Diethylpropion hydrochloride 75 mg (controlled release) tablets: One tablet daily, swallowed whole, in mid-morning.

HOW SUPPLIED

Diethylpropion hydrochloride 75 mg tablets are oval, white, domed, imprinted “2690V” on one side and plain on the other.

Diethylpropion hydrochloride 75 mg tablets are supplied in bottles of 100 and 250.

Dispense in a tight, light-resistant container as defined in the USP with a child-resistant closure. Store at controlled room temperature, 15°- 30°C (59°- 86°F).

CAUTION:

Federal law prohibits dispensing without prescription.

Manufactured by:
3M Pharmaceuticals
Northridge, CA 91324

Manufactured for:
Qualitest Products, Inc.

IN99
Rev 2/95
R1